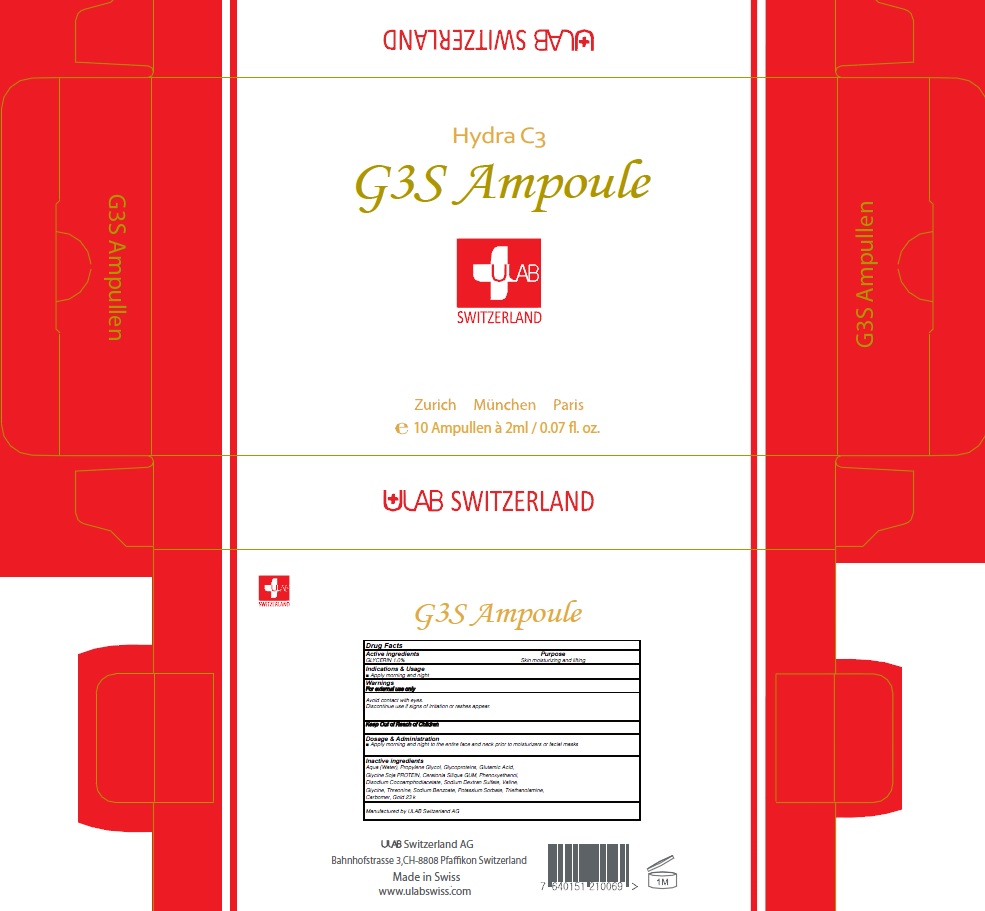 DRUG LABEL: G3S AMPOULE
NDC: 71276-110 | Form: LIQUID
Manufacturer: ULAB
Category: otc | Type: HUMAN OTC DRUG LABEL
Date: 20170322

ACTIVE INGREDIENTS: GLYCERIN 0.02 g/2 mL
INACTIVE INGREDIENTS: Water; Propylene Glycol

ACTIVE INGREDIENT

Active ingredients: GLYCERIN 1.0%

INACTIVE INGREDIENT

Inactive ingredients: Aqua (Water), Propylene Glycol, Glycoproteins, Glutamic Acid, Glycine Soja PROTEIN, Ceratonia Siliqua GUM, Phenoxyethanol, Disodium Cocoamphodiacetate, Sodium Dextran Sulfate, Valine, Glycine, Threonine, Sodium Benzoate, Potassium Sorbate, Triethanolamine, Carbomer, Gold 23 k

PURPOSE

Purpose: Skin moisturizing and lifting

WARNINGS

Warnings: For external use only Avoid contact with eyes. Discontinue use if signs of irritation or rashes appear.

KEEP OUT OF REACH OF CHILDREN

INDICATIONS & USAGE

Indications & Usage: Apply morning and night

DOSAGE & ADMINISTRATION

Dosage & Administration: Apply morning and night to the entire face and neck prior to moisturizers or facial masks